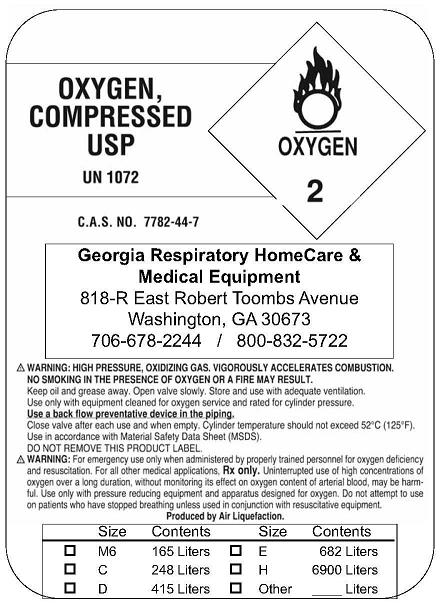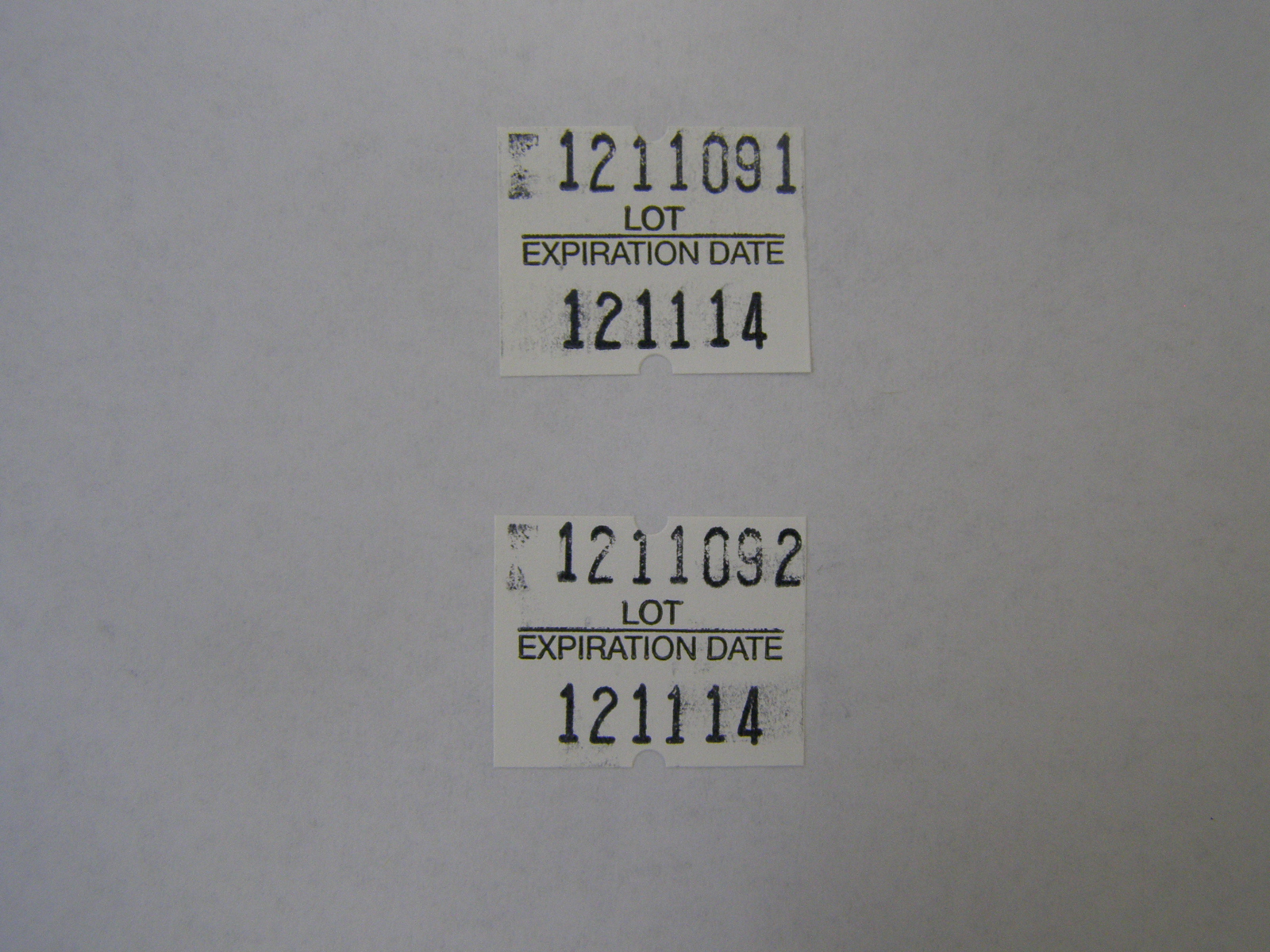 DRUG LABEL: Oxygen
NDC: 16408-2714 | Form: GAS
Manufacturer: Georgia Respiratory HomeCare & Medical Equipment LLC
Category: prescription | Type: HUMAN PRESCRIPTION DRUG LABEL
Date: 20091224

ACTIVE INGREDIENTS: Oxygen 99 L/100 L

Oxygen